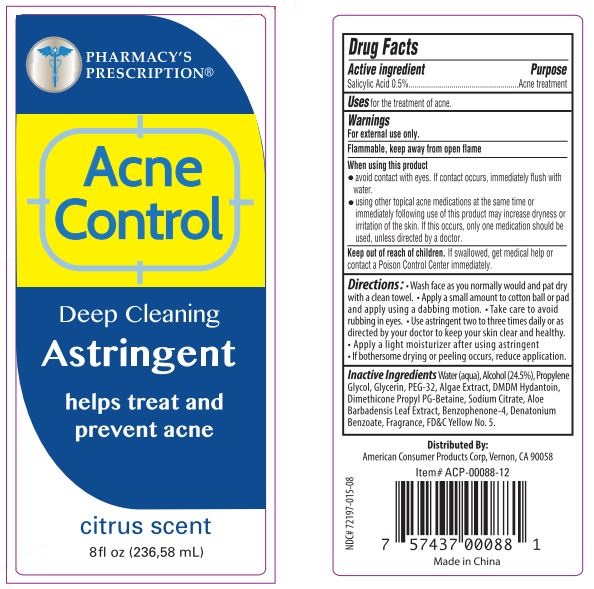 DRUG LABEL: Pharmacys Prescription 8 OZ Acne Control
NDC: 72197-015 | Form: LIQUID
Manufacturer: American Consumer Products Corp
Category: otc | Type: HUMAN OTC DRUG LABEL
Date: 20190916

ACTIVE INGREDIENTS: SALICYLIC ACID 0.05 g/100 mL
INACTIVE INGREDIENTS: ALCOHOL; POLYETHYLENE GLYCOL 1600; ALOE VERA LEAF; SULISOBENZONE; PHYMATOLITHON CALCAREUM; FD&C YELLOW NO. 5; PROPYLENE GLYCOL; GLYCERIN; DMDM HYDANTOIN; DIMETHICONE; WATER; SODIUM CITRATE; DENATONIUM BENZOATE

Pharmacys Prescription 8 OZ Acne Control

Active Ingredient

Active ingredient: Salicylic Acid 0.5%

Purpose

Purpose: Acne treatment

Uses: for the treatment of acne.

Warnings

Warnings: For external use only.

Flammable, keep away from open flame.

Keep out of reach of children: If swallowed, get medical help or contact a Poison Control Center immediately.

Inactive Ingredients

Water (aqua), Alcohol (24.5%), Propylene Glycol, Glycerin, PEG-32, Algae Extract, DMDM Hydantoin, Dimethicone Propyl PG-Betaine, Sodium Citrate, Aloe Barbadensis Leaf Extract, Benzophenone-4, Denatonium Benzoate, Fragrance, FD&C Yellow No..5.

Directions

Directions: Wash face as you normally would and pat dry with a clean towel. Apply a small amount to cotton ball or pad and applyu using a dabbing motion. Take care to avoid rubbing in eyes. Use astringent two to three times daily or as directed by your doctor to keep your skin clear and healthy. Apply a light moisturizer after using astringent.

When using this product

- avoid contact with eyes. If contact occurs, immediately flush with water.

- using other topical acne medications at the same time or immediately following use of this product may increase dryness or irritation of the skin. If this occurs, only one medication should be used, unless directed by a doctor.

Indications & Usage

If bothersome drying or peeling occurs, reduce application.